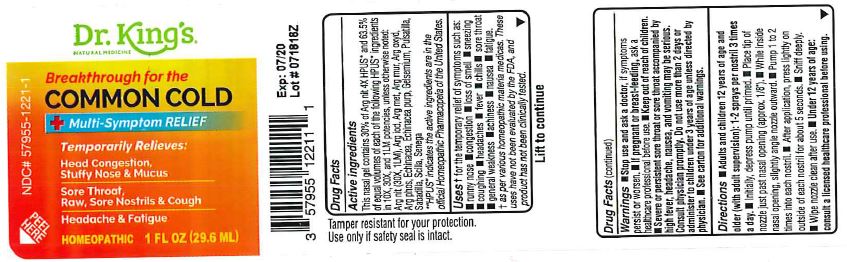 DRUG LABEL: Common Cold
NDC: 57955-1221 | Form: GEL
Manufacturer: King Bio Inc
Category: homeopathic | Type: HUMAN OTC DRUG LABEL
Date: 20181211

ACTIVE INGREDIENTS: SILVER NITRATE 30 [hp_X]/30 mL; SILVER IODIDE 10 [hp_X]/30 mL; SILVER 10 [hp_X]/30 mL; SILVER CHLORIDE 10 [hp_X]/30 mL; SILVER OXIDE 10 [hp_X]/30 mL; SILVER PHOSPHATE 10 [hp_X]/30 mL; ECHINACEA, UNSPECIFIED 10 [hp_X]/30 mL; ECHINACEA PURPUREA 10 [hp_X]/30 mL; GELSEMIUM SEMPERVIRENS ROOT 10 [hp_X]/30 mL; ANEMONE PULSATILLA 10 [hp_X]/30 mL; SCHOENOCAULON OFFICINALE SEED 10 [hp_X]/30 mL; DRIMIA MARITIMA BULB 10 [hp_X]/30 mL; POLYGALA SENEGA ROOT 10 [hp_X]/30 mL
INACTIVE INGREDIENTS: ALOE VERA LEAF; METHYL SALICYLATE; WATER; EUCALYPTUS OIL; GLYCERIN; SODIUM COCOYL GLUTAMATE; HYALURONATE SODIUM; STEVIOL; XANTHAN GUM; GINGER OIL

Common Cold

Active Ingredients

This nasal ge lconains 80% of Arg nit 4X HPUS and 63.5% of equal volumes of each of the remaining HPUS ingredients in 10X, 30X, and 1LM potencies, unless otherwise noted.

Argentum nitricum, Argentum iodatum, Argentum metallicum, Argentum muriaticum, Argentum oxydatum, Argentum phosphoricum, Echinacea, Enchinacea purpurea, Gelsemium sempervirens, Pulsatilla, Sabadilla, Scilla maritima, Senega officinalis

Inactive Ingredients

Aloe barbadensis leaf juice, Betula lenta bark oil, Bio-Energetically Enhanced pure water, Eucalyptus globulus leaf oil, glycerin, sodium cocoyl glutamate, sodiumhyaluronate, steviol, xanthan gum, Zingiber officinale (ginger) root oil.

Directions

Adults and children 12 years of age and older(with adult supervision): 1-2 sprays per nostril 3 times a day.

Initially, depress pumountil primed. Place tip of nozzle just past nasal opening (approx 1/8") While inside nasal opening, slightly angle nozzle outward. Pump 1 to 2 times into each nostril. After application, press lightly on on outside of each nostril for about 5 seconds. Sniff deeply. Wipe nozzle clean after use. Under 12 years of age: consult a healthcare professional before using.

Purpose

Argentum nitricum (30X, 1LM)............congestion, loss of smell, fever

Argentum iodatum.............................hoarseness

Argentum metallicum..........................mucus, stuffy nose, sneezing

Argentum muriaticum.........................headache

Argentum oxydatum...........................nausea, mucus membrane affections

Argentum phosphoricum.....................swelling

Echinacea.........................................raw and sore nostrils

Enchinacea purpurea..........................nasal congestion, fever

Gelsemium sempervirens....................weakness, achiness, fatigue, chills

Pulsatilla...........................................cough, loss of smell, sore nose

Sabadilla...........................................sneezing, sore throat

Scilla maritima...................................runny nose

Senega officinalis................................headache

Warnings

For nasal use only. Ask a doctor before use if you have had recent nose ulcers or surgery, have had a nose injury that has not healed. When using this product, use of spray by more than one person may spread infection. Clean tip after use temporary discomfort such as minor burning, stinging, sneezing or an increase in nasal discharge may occur. Stop use and ask a doctor, if symptoms persist or worsen. Ifpregnant or breast-feeding, ask a healthcare professional before use.Keep out of reach of children. If swallowed get medical help or contact a Poison Control Center right away. Severe or persistent sore throat or sore throat accompanied by high fever, headache, nausea and vomiting may be serious. Consult a physician promptly. Do not use more than 2 days or administer to children under 3 years of age unless directed by a physician.

Keep out of reach of children.

Other Information

This product is intended to compliment not replace, standard medical care. Tamper resistant for your protection. Use only if safety seal is intact. Store at room temperature.

Uses

for the temporary relief of symptoms sucha as:

runny nose, congestion, loss of smell, sneezing, coughing, headaches, fever, chills, sore throat, general weakness, achiness, nausea, fatigue

as per various homeopathis materia medicas. These uses have not been evaluated by the FDA, and product has not been clinically tested.